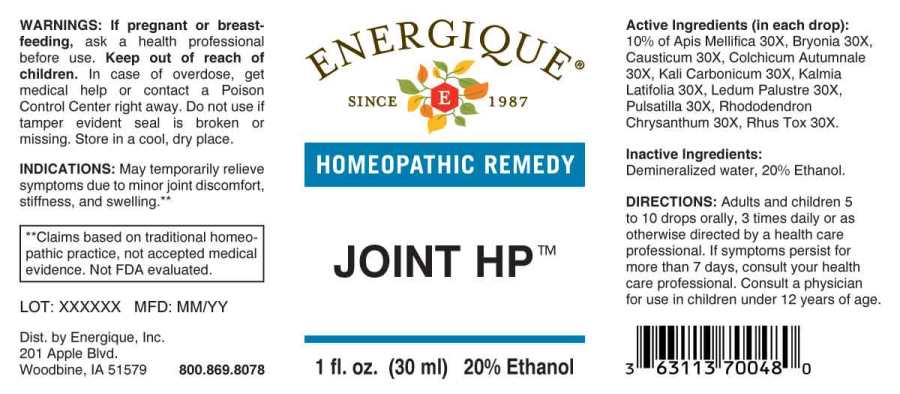 DRUG LABEL: Joint HP
NDC: 44911-0585 | Form: LIQUID
Manufacturer: Energique, Inc.
Category: homeopathic | Type: HUMAN OTC DRUG LABEL
Date: 20240326

ACTIVE INGREDIENTS: APIS MELLIFERA 30 [hp_X]/1 mL; BRYONIA ALBA ROOT 30 [hp_X]/1 mL; CAUSTICUM 30 [hp_X]/1 mL; COLCHICUM AUTUMNALE BULB 30 [hp_X]/1 mL; POTASSIUM CARBONATE 30 [hp_X]/1 mL; KALMIA LATIFOLIA LEAF 30 [hp_X]/1 mL; LEDUM PALUSTRE TWIG 30 [hp_X]/1 mL; PULSATILLA PRATENSIS WHOLE 30 [hp_X]/1 mL; RHODODENDRON AUREUM LEAF 30 [hp_X]/1 mL; TOXICODENDRON PUBESCENS LEAF 30 [hp_X]/1 mL
INACTIVE INGREDIENTS: WATER; ALCOHOL

DRUG FACTS;

ACTIVE INGREDIENTS:

(in each drop): 10% of Apis Mellifica 30X, Bryonia (Alba) 30X, Causticum 30X, Colchicum Autumnale 30X, Kali Carbonicum 30X, Kalmia Latifolia 30X, Ledum Palustre 30X, Pulsatilla (Pratensis) 30X, Rhododendron Chrysanthum 30X, Rhus Tox 30X.

INDICATIONS:

May temporarily relieve symptoms due to minor joint inflammation and swelling.**

**Claims based on traditional homeopathic practice, not accepted medical evidence. Not FDA evaluated.

WARNINGS:

If pregnant or breast-feeding, ask a health professional before use.

Keep out of reach of children. In case of overdose, get medical help or contact a Poison Control Center right away.

Do not use if tamper evident seal is broken or missing.

Store in a cool, dry place.

KEEP OUT OF REACH OF CHILDREN:

In case of overdose, get medical help or contact a Poison Control Center right away.

DIRECTIONS:

Adults and children 5 to 10 drops orally, 3 times daily or as otherwise directed by a health care professional. If symptoms persist for more than 7 days, consult your health care professional. Consult a physician for use in children under 12 years of age.

INDICATIONS:

May temporarily relieve symptoms due to minor joint inflammation and swelling.**

**Claims based on traditional homeopathic practice, not accepted medical evidence. Not FDA evaluated.

INACTIVE INGREDIENTS:

Demineralized water, 20% Ethanol.

QUESTIONS:

Dist by Energique, Inc.

201 Apple Blvd

Woodbine, IA 51579

800.869.8078

PACKAGE LABEL DISPLAY:

ENERGIQUE

SINCE 1987

HOMEOPATHIC REMEDY

JOINT HP

1 fl. oz. (30 ml)